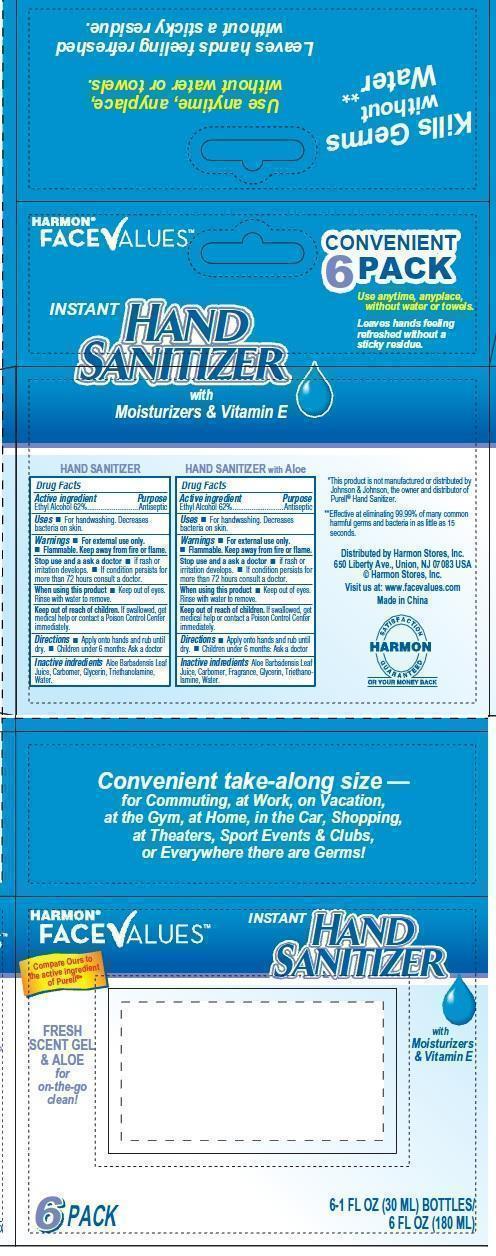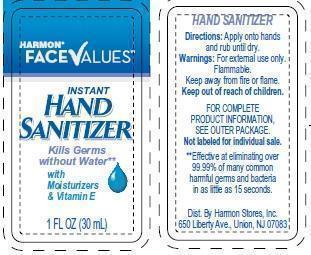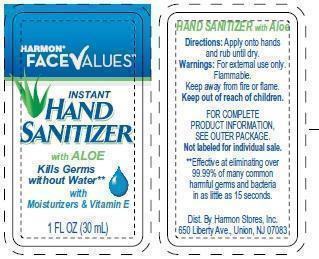 DRUG LABEL: Instant Hand Sanitizer Convenience Pack
NDC: 63940-600 | Form: KIT | Route: TOPICAL
Manufacturer: Harmon Stores Inc
Category: otc | Type: HUMAN OTC DRUG LABEL
Date: 20181108

ACTIVE INGREDIENTS: ALCOHOL 620 mg/1 mL; ALCOHOL 620 mg/1 mL
INACTIVE INGREDIENTS: ALOE VERA LEAF; GLYCERIN; TROLAMINE; WATER; ALOE VERA LEAF; GLYCERIN; TROLAMINE; WATER

Instant Hand Sanitizer 6 pack

Active Ingredient

Ethyl Alcohol 62%

Purpose

Antiseptic

Uses

For handwashing. Decreases bacteria on skin

Warnings

For external use only

Flammable. Keep away from fire or flame

Stop use and ask a doctor

if rash or irritation develops

if condition persists for more than 72 hours consult a doctor

Keep out of reach of children

If swallowed, get medical help or contact a Poison Control Center immediately

Directions

Apply onto hands and rub until dry

Children under 6 months: Ask a doctor

Inactive Ingredients

Aloe barbadensis Leave Juice, Carbomer, Fragrance, Glycerin, Triethanolamine, Water